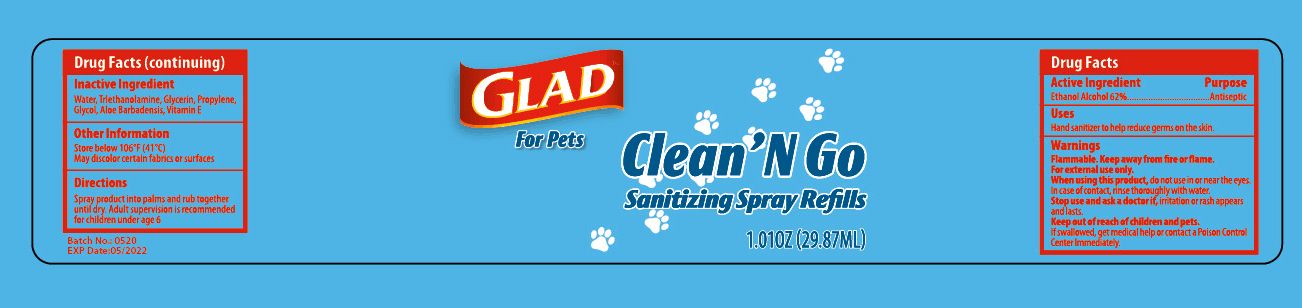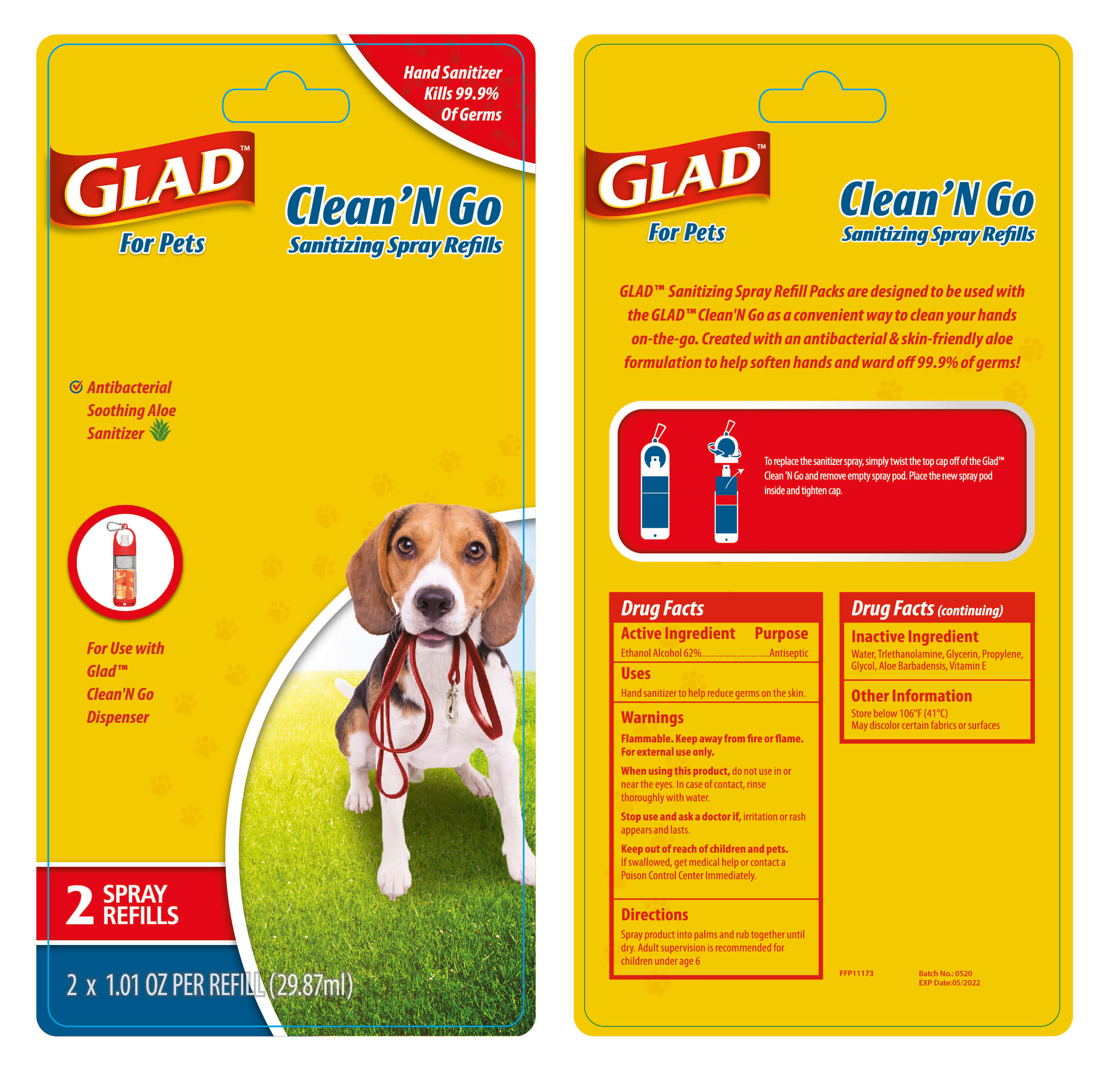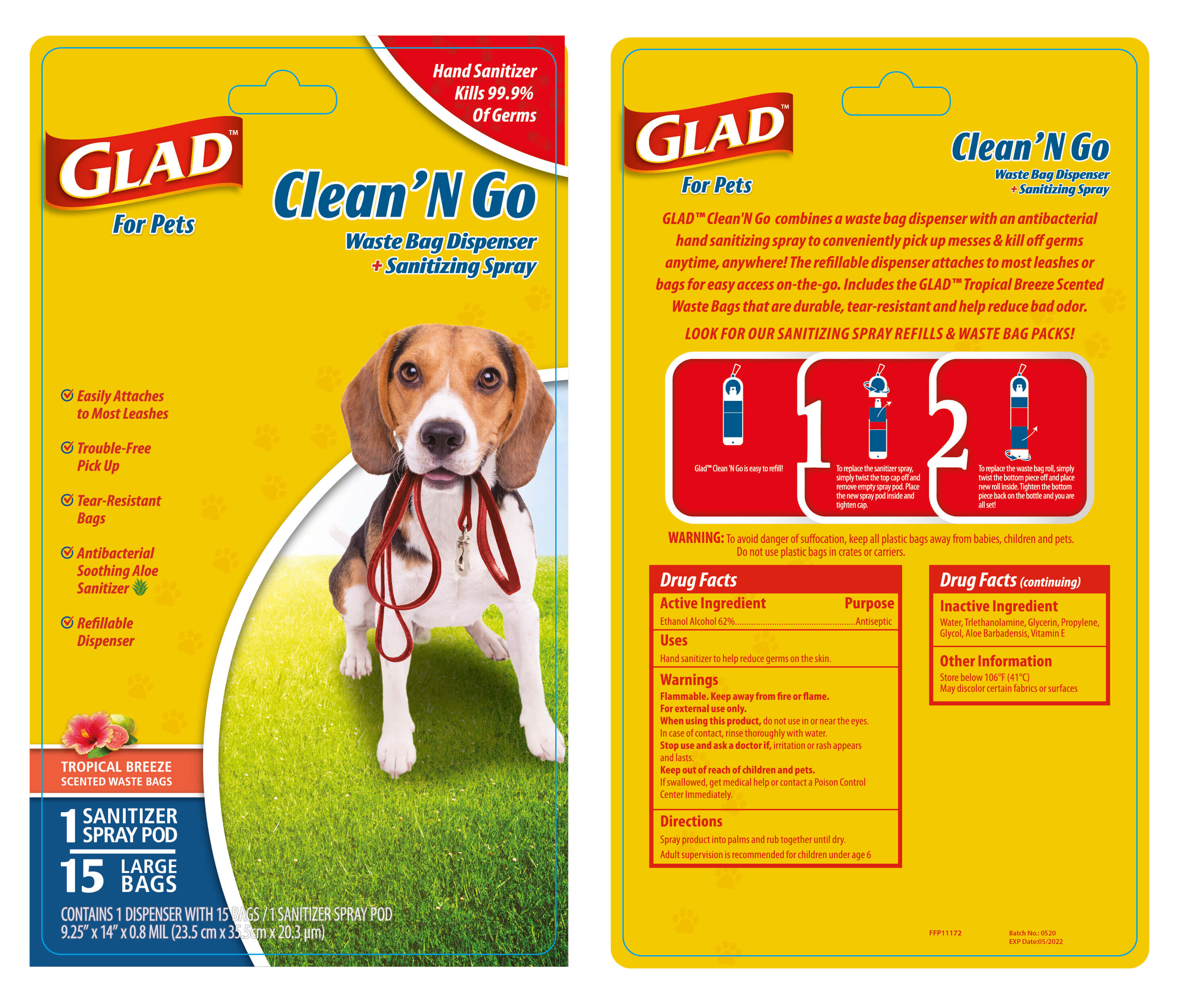 DRUG LABEL: HAND SANITIZER
NDC: 47993-293 | Form: GEL
Manufacturer: NINGBO JIANGBEI OCEAN STAR TRADING CO.,LTD
Category: otc | Type: HUMAN OTC DRUG LABEL
Date: 20201105

ACTIVE INGREDIENTS: ALCOHOL 62 g/112 mL
INACTIVE INGREDIENTS: WATER; TRIETHANOLAMINE BENZOATE; GLYCERIN; PROPYLENE; ETHYLENE GLYCOL; ALOE VERA LEAF; TOCOPHEROL

47993-293

Active ingredients

Ethanol Alcohol 62%

PURPOSE

Antiseptic

Uses：

Hand sanitizer to help reduce germs on the skin.

Warnings:

Flammable. Keep away from fire or flame. For external use only.

When using this product, do not use in or near the eyes. In case of contact, rinse thoroughly with water.

Stop use and ask a doctor if, irritation or rash appears and lasts.

Keep out of reach of children and pets. If swallowed, get medical help or contact a Poison Control Center Immediately.

INACTIVE INGREDIENT

Inactive Ingredients: Water,Triethanolamine,Glycerin,Propylene,Glycol,Aloe barbadensis,Vitamin E

Other information

Store below 106℉(41℃)

May discolor certain fabrics or surface

Directions:

Spray product into palms and rub together until dry.

Adult supervision is recommended for children under age 6.